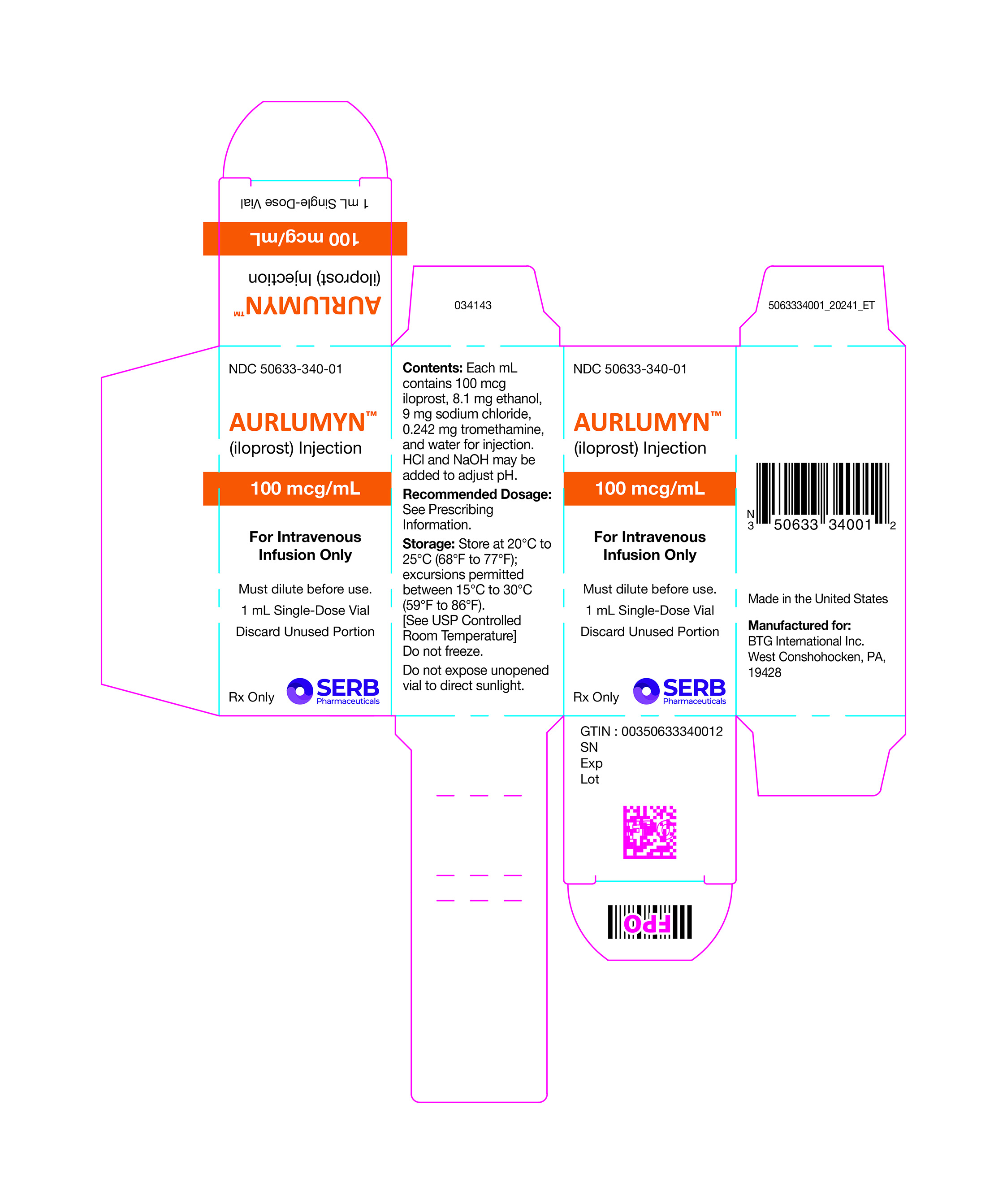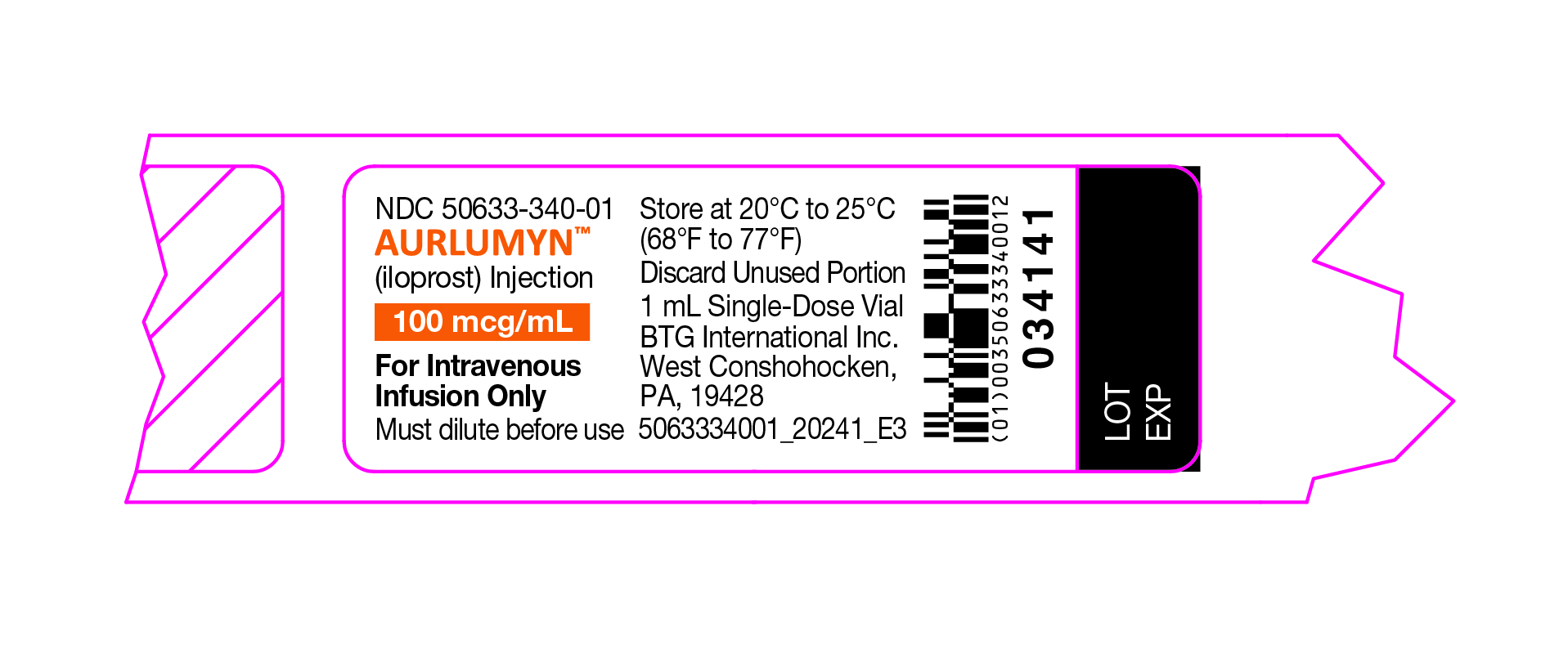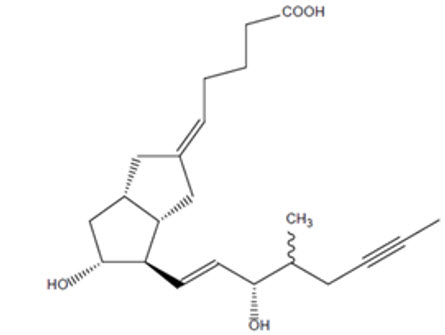 DRUG LABEL: AURLUMYN
NDC: 50633-340 | Form: INJECTION, SOLUTION
Manufacturer: BTG International Inc
Category: prescription | Type: HUMAN PRESCRIPTION DRUG LABEL
Date: 20250101

ACTIVE INGREDIENTS: ILOPROST 100 ug/1 mL
INACTIVE INGREDIENTS: ALCOHOL 8.1 mg/1 mL; SODIUM CHLORIDE 9 mg/1 mL; TROMETHAMINE 0.242 mg/1 mL; WATER; HYDROCHLORIC ACID; SODIUM HYDROXIDE

HIGHLIGHTS OF PRESCRIBING INFORMATION

These highlights do not include all the information needed to use AURLUMYN safely and effectively. See full prescribing information for AURLUMYN.
AURLUMYNTM(iloprost) injection, for intravenous use
Initial U.S. Approval: 2004

1 INDICATIONS AND USAGE

AURLUMYN is a prostacyclin mimetic indicated for the treatment of severe frostbite in adults to reduce the risk of digit amputations. Effectiveness was established in young, healthy adults who suffered frostbite at high altitudes (1.1).

2 DOSAGE AND ADMINISTRATION

- Initiate intravenous infusion at 0.5 ng/kg/minute and titrate in 0.5 ng/kg/minute increments based on tolerability at intervals of 30 minutes to a maximum of 2 ng/kg/minute (2.1).
- Administer as continuous infusion for 6 hours each day up to a maximum of 8 consecutive days (2.1).
- Patients with moderate or severe hepatic impairment (Child-Pugh Class B or C): initiate infusion at 0.25 ng/kg/minute and titrate as described above (2.3).
- Patients with renal impairment with eGFR less than 30 mL/min: initiate infusion at 0.5 ng/kg/minute and titrate as described above. If the patient cannot tolerate the starting dose of 0.5 ng/kg/minute, the dose can be decreased to 0.25 ng/kg/minute (2.4).
- See Full Prescribing Information for instructions on preparation and administration (2.2).

3 DOSAGE FORMS AND STRENGTHS

- Injection: 100 mcg per mL in a single dose vial (3).

4 CONTRAINDICATIONS

- None (4).

5 WARNINGS AND PRECAUTIONS

- AURLUMYN may cause symptomatic hypotension. Monitor vital signs while initiating AURLUMYN. Correct hypotension prior to administration of AURLUMYN (5.1).

6 ADVERSE REACTIONS

Most common adverse events include headache, flushing, palpitations/tachycardia, nausea, vomiting, dizziness, and hypotension (6.1).

To report SUSPECTED ADVERSE REACTIONS, contact BTG International, Inc. at 1-877-377-3748 or FDA at 1-800-FDA-1088 or www.fda.gov/medwatch.

8 USE IN SPECIFIC POPULATIONS

- Lactation: Advise not to breastfeed (8.2).

FULL PRESCRIBING INFORMATION

1 INDICATIONS AND USAGE

1.1 Frostbite

AURLUMYN is indicated for the treatment of severe frostbite in adults to reduce the risk of digit amputations. Effectiveness was established in young, healthy adults who suffered frostbite at high altitudes.

2 DOSAGE AND ADMINISTRATION

2.1 Recommended Dosage

Monitor vital signs prior to the start of the infusion and with every dose increase.

Administer AURLUMYN as a continuous intravenous infusion over 6 hours each day for up to a maximum of 8 consecutive days.

Start the initial infusion on day 1 at a rate of 0.5 ng/kg/minute and increase in increments of 0.5 ng/kg/minute every 30 minutes according to tolerability up to 2 ng/kg/minute. Dosage is based on actual patient body weight (kg). Repeat dose titration steps on day 2 and day 3. From day 4 onward, start the infusion at the highest tolerated dose from the previous day, and adjust the rate as needed, based on tolerability.

Adverse reactions such as headache, flushing, jaw pain, myalgia, nausea, and vomiting may be dose-limiting. If dose-limiting adverse reactions occur that cannot be tolerated by the patient, then decrease the dose in a stepwise manner by 0.5 ng/kg/min every 30 minutes, until a tolerated dose is reached. If a dose-limiting adverse reaction occurs during administration of AURLUMYN at the starting dose, the infusion should be discontinued, and re-initiation of the infusion can be attempted after the event has resolved or been treated. If infusion is stopped at any point for a dose-limiting adverse event, infusion can be reinitiated at a previously tolerated dose/infusion rate once the event has resolved. The maximum tolerated dose should be maintained for the remaining 6-hour daily infusion.

2.2 Preparation and Administration

Preparation:

Use aseptic technique to prepare AURLUMYN.

Inspect the vial for particulate matter prior to administration. Do not use if the solution is discolored or cloudy or if foreign particles are present.

Dilution:

AURLUMYN should only be diluted using 0.9% Sodium Chloride Injection, USP. Do not dilute or mix AURLUMYN with any other parenteral medications or solutions prior to or during administration.

Withdraw 1 mL (100 mcg) of AURLUMYN solution from the vial and transfer into 100 mL of 0.9% Sodium Chloride Injection, USP polyvinyl chloride (PVC) infusion bag to make a final concentration of 1 mcg/mL (1,000 ng/mL). AURLUMYN can be added to commercially available infusion bags labeled to contain 100 mL of 0.9% Sodium Chloride Injection, USP.

Gently mix the intravenous bag by slowly inverting the bag. Do not shake.

Parenteral drug products should be inspected visually for particulate matter and discoloration prior to administration, whenever solution and container permit. Do not use if visibly opaque particles, discoloration, or foreign particles are observed.

Immediately use diluted AURLUMYN infusion solution. If not used immediately, the diluted solution can be stored at room temperature (20°C to 25°C [68°F to 77°F]) for up to 4 hours.

Administration

Administer AURLUMYN as an intravenous infusion through a peripheral line or peripherally inserted central catheter using an infusion pump.

Use an infusion set with an in-line 0.22- or 0.2-micron filter.

Once diluted, AURLUMYN should be administered with an infusion pump that can support the minimum and maximum flow rates. The infusion pump used to administer AURLUMYN should: (1) be able to deliver rates 0.1 to 99.9 mL per hour, (2) adjust infusions rates with increments of 0.1 mL per hour, (3) be accurate to within 5% of programmed rate, and (4) be positive pressure-driven (continuous or pulsatile). The reservoir and infusion line set should be made of polyvinyl chloride.

Infusion rates may be calculated using the following formula:

Infusion Rate (mL/hr) = [Dose (ng/kg/min) × Weight (kg) × 60 min/hr]
Final Concentration (1,000 ng/mL)

Avoid inadvertent administration of a bolus of the drug. Do not flush the catheter without withdrawing residual drug from the catheter system.

Discard any unused portion.

2.3 Use in Patients with Hepatic Impairment

Patients with moderate or severe hepatic impairment (Child-Pugh Class B or C): Initiate dosage at 0.25 ng/kg/minute for 30 minutes then continue titration in 0.5 ng/kg/minutes increments every 30 minutes according to tolerability to a maximum dose of 2 ng/kg/minute [see Use in Specific Populations (8.6)] .

2.4 Use in Patients with Renal Impairment

Patients with renal impairment with eGFR less than 30 mL/min: Initiate and titrate dosing per recommended dosage. If patient cannot tolerate the starting dose of 0.5 ng/kg/minute the dose can be lowered to 0.25 ng/kg/minute. The effect of dialysis on iloprost exposure has not been evaluated. For patients requiring intermittent hemodialysis, consider iloprost administration after the end of hemodialysis. Alternatively, hemodialysis can be started at least one hour after the end of iloprost infusion.

3 DOSAGE FORMS AND STRENGTHS

Injection: 100 mcg per mL iloprost as a clear and colorless solution in a single-dose vial.

4 CONTRAINDICATIONS

None.

5 WARNINGS AND PRECAUTIONS

5.1 Hypotension

AURLUMYN is a systemic vasodilator and may cause symptomatic hypotension. Correct hypotension prior to administration of AURLUMYN. Monitor vital signs while administering AURLUMYN. Consider temporary discontinuation of concomitant vasodilator or other antihypertensive medications while administering AURLUMYN to reduce potential additive hypotensive effects. Consider down-titration or discontinuation of AURLUMYN if hypotension persists despite discontinuation of other antihypertensives and fluid resuscitation.

6 ADVERSE REACTIONS

6.1 Clinical Studies Experience

Because clinical trials are conducted under widely varying conditions, adverse reaction rates observed in the clinical trials of a drug cannot be directly compared to rates in the clinical trials of another drug and may not reflect the rates observed in practice.

Adverse events reported with the use of intravenous iloprost in patients with frostbite from the published literature include headache, flushing, palpitations/tachycardia, nausea, vomiting, dizziness, and hypotension.

Pre-marketing safety data on AURLUMYN were obtained from 116 patients with Systemic Sclerosis receiving iloprost in 2 multicenter, double-blind, randomized, placebo-controlled studies in patients with Systemic Sclerosis experiencing symptomatic digital ischemic episodes (Raynaud's Phenomenon). Patients received intravenous AURLUMYN administered as a continuous infusion over 6 hours each day for 5 consecutive days and the dose was adjusted according to individual tolerability within the range of 0.5 to 2.0 ng /kg /min. The observed safety profile in these patients was similar to that observed with IV iloprost.

8 USE IN SPECIFIC POPULATIONS

8.1 Pregnancy

Risk Summary

There are no available data with AURLUMYN during pregnancy to evaluate for a drug-associated risk of major birth defects, miscarriage, or adverse maternal or fetal outcomes. There are limited published cases of inhaled iloprost use during pregnancy, primarily during the second and third trimesters, that have not identified a drug-associated risk of adverse maternal or fetal outcomes. In animal reproductive studies, administration of continuous intravenous iloprost to pregnant Han-Wistar rats during organogenesis at doses 2-times the maximum recommended human dose on a mg/m^2basis resulted in adverse developmental outcomes. However, there were no adverse developmental outcomes with oral or intravenous administration of iloprost to pregnant Sprague-Dawley rats, rabbits, and monkeys at doses 1111-, 1061-, and 12-times, respectively, the maximum recommended human dose by Cmax (see Data).

The background risk of major birth defects and miscarriage for the indicated populations is unknown. All pregnancies have a background risk of birth defect, loss, or other adverse outcomes. In the US general population, the estimated background risk of major birth defects and miscarriage in clinically recognized pregnancies is 2 to 4% and 15 to 20%, respectively.

Data

Animal Data

In developmental toxicity studies in pregnant Han-Wistar rats, continuous intravenous administration of iloprost at a dosage of 0.01 mg/kg daily (2 times the maximum recommended human dose on a mg/m^2basis, serum levels not available) led to shortened digits of the thoracic extremity in fetuses and pups. In similar studies in pregnant Sprague-Dawley rats that received iloprost clathrate (13% iloprost by weight) orally at dosages of up to 50 mg/kg/day (Cmaxof 90 ng/mL), in pregnant rabbits at intravenous dosages of up to 0.5 mg/kg/day (Cmaxof 86 ng/mL), and in pregnant monkeys at dosages of up to 0.04 mg/kg/day (serum levels of 1 ng/mL), at 1111-, 1062- and 12-times, respectively, the maximum recommended human dose by Cmax, no such digital anomalies or other gross-structural abnormalities were observed in the fetuses/pups. However, in gravid Sprague-Dawley rats, iloprost clathrate (13% iloprost) significantly increased the number of non-viable fetuses at a maternally toxic oral dosage of 250 mg/kg/day (729 times the maximum recommended human dose on a mg/m^2basis) and in Han-Wistar rats was found to be embryolethal in 15 of 44 litters at an intravenous dosage of 1 mg/kg/day (225 times the maximum recommended human dose on a mg/m^2basis).

8.2 Lactation

Risk Summary

There are no data on the presence of iloprost in human milk, the effects on the breastfed infant, or the effects on milk production. Iloprost is present in rat milk (see Data). When a drug is present in animal milk, it is likely that the drug will be present in human milk. Because of the potential for serious adverse reactions, advise women not to breastfeed during treatment with iloprost [see Warnings and Precautions (5) and Adverse Reactions (6)] .

Data

In studies with Han-Wistar rats, higher mortality was observed in pups of lactating dams receiving iloprost intravenously at 1 mg/kg daily (at 225 times the maximum recommended human dose on a mg/m^2basis). In Sprague-Dawley rats, higher mortality was also observed in nursing pups at a maternally toxic oral dose of 250 mg/kg/day of iloprost clathrate (13% iloprost by weight) (729 times the maximum recommended human dose on a mg/m^2basis). In rats, a passage of low levels of iloprost or metabolites into the milk was observed (less than 1% of iloprost dose given intravenously). No disturbance of post-natal development and reproductive performance was seen in animals exposed during lactation.

8.4 Pediatric Use

Safety and efficacy in pediatric patients have not been established.

8.5 Geriatric Use

Clinical studies of iloprost did not include sufficient numbers of subjects aged 65 years and older to determine whether they respond differently than younger subjects. Other reported clinical experience with iloprost has not identified differences in responses between elderly and younger patients. In general, dose selection for an elderly patient should be cautious, usually starting at the low end of the dosing range, reflecting the greater frequency of decreased hepatic, renal, or cardiac function, and of concomitant disease or other drug therapy.

8.6 Hepatic Impairment

In an intravenous iloprost study in patients with liver cirrhosis, the mean clearance in Child-Pugh Class B subjects (n = 5) was approximately 10 mL/min/kg (half that of healthy subjects based on a cross study comparison). In patients with moderate or severe hepatic impairment (Child-Pugh Class B or C), use a lower starting dose of 0.25 ng/kg/minute [see Dosage and Administration (2.3)].

8.7 Renal Impairment

In a study of intravenous infusion of iloprost on a dialysis-free day in adults with kidney failure receiving intermittent hemodialysis treatment (n = 7), the mean AUC0-4hwas 230 pg*h/mL compared to 54 pg*h/mL in patients with kidney failure (n = 8) not requiring intermittent dialysis. The half-life was similar in both groups. The mean AUC0-4hwas 48 pg*h/mL in normal subjects in a different study. In patients with renal impairment with eGFR less than 30 mL/min, the dose can be lowered to 0.25 ng/kg/minute if the patient cannot tolerate the starting dose of 0.5 ng/kg/minute [see Dosage and Administration (2.4)].

The effect of dialysis on the clearance of iloprost has not been evaluated. For patients requiring intermittent hemodialysis, consider iloprost administration after the end of hemodialysis. Alternatively, hemodialysis can be started at least one hour after the end of iloprost infusion.

10 OVERDOSAGE

Cases of overdose of intravenous iloprost have not been reported. Hypotension, vomiting, and diarrhea are likely. A specific antidote is not known. Interruption of the infusion session, monitoring, and symptomatic measures are recommended.

11 DESCRIPTION

AURLUMYN contains iloprost, a synthetic analog of prostacyclin PGI2. The chemical name for iloprost is (5 E)-[3a S,4 R,5 R,6a S)-5-hydroxy-4-[(1 E)-(3 S,4 RS)-3-hydroxy-4-methyloct-1-en-6-ynyl]-hexahydropentalen-2(1 H)-ylidene]pentanoic acid. Iloprost consists of a mixture of the 4R and 4S diastereoisomers at a ratio of approximately 53:47. Iloprost is an oily substance, which is soluble in methanol, ethanol, ethyl acetate, acetone, and pH 7 buffer, sparingly soluble in buffer pH 9, and very slightly soluble in distilled water, buffer pH 3, and buffer pH 5. The molecular formula of iloprost is C22H32O4and its molecular weight is 360.49. The structural formula is shown below:

AURLUMYN (iloprost) injection is a clear, colorless, sterile solution formulated for intravenous use. AURLUMYN is supplied in single-use glass vials containing 1-mL per vial. Each mL of the solution contains 100 mcg (0.1 mg) of iloprost as the active ingredient and the following inactive ingredients: 8.1 mg ethanol, 9 mg sodium chloride, and 0.242 mg tromethamine. Hydrochloric acid and sodium hydroxide is added to adjust pH to 8.3.

The solution contains no preservatives.

12 CLINICAL PHARMACOLOGY

12.1 Mechanism of Action

Iloprost is a synthetic analog of prostacyclin PGI2. Iloprost is a vasodilator and inhibits platelet aggregation.

12.3 Pharmacokinetics

General

Iloprost administered intravenously has linear pharmacokinetics over the dose range of 1 to 3 ng/kg/min. The half-life of iloprost is 20 to 30 minutes.

Absorption and Distribution

Following intravenous infusion, the apparent steady-state volume of distribution was 0.7 to 0.8 L/kg in healthy subjects. Iloprost is approximately 60% protein-bound, mainly to albumin, and this ratio is concentration-independent in the range of 30 to 3000 pg/mL.

Metabolism and Excretion

In vitro studies reveal that cytochrome P450-dependent metabolism plays only a minor role in the biotransformation of iloprost. Iloprost is metabolized principally via β-oxidation of the carboxyl side chain. The main metabolite is tetranor-iloprost, which is found in the urine in free and conjugated form. In animal experiments, tetranor-iloprost was pharmacologically inactive.

Clearance in normal subjects was approximately 20 mL/min/kg.

A mass-balance study using intravenously and orally administered [^3H]-iloprost in healthy subjects (n = 8) showed recovery of 81% of total radioactivity over 14 hours post-dose, with 68% and 12% recoveries in urine and feces, respectively.

Drug Interactions

Intravenous infusion of iloprost had no effect on the pharmacokinetics of digoxin. Acetylsalicylic acid did not alter the clearance (pharmacokinetics) of iloprost.

13 NONCLINICAL TOXICOLOGY

13.1 Carcinogenesis, Mutagenesis, Impairment of Fertility

Iloprost was not mutagenic in bacterial and mammalian cells in the presence or absence of extrinsic metabolic activation. Iloprost did not cause chromosomal aberrations in vitro in human lymphocytes and was not clastogenic in vivoin NMRI/SPF mice. There was no evidence of a tumorigenic effect of iloprost clathrate (13% iloprost by weight) in Sprague-Dawley rats dosed orally for up to 8 months at doses of up to 125 mg/kg/day (Cmaxof 45 ng/mL serum, 556 times the Cmaxat maximum recommended human dose), followed by 16 months at 100 mg/kg/day , or in Crl:CD-1®(ICR)BR albino mice dosed orally for up to 24 months at doses of up to 125 mg/kg/day (Cmaxof 156 ng/mL serum, 1926 times the Cmax at maximum recommended human dose). The recommended clinical dosage regimen for iloprost (2 ng/kg/min) affords a serum Cmaxof 0.081 ng/mL. Fertility of males or females was not impaired in Han-Wistar rats at intravenous doses up to 1 mg/kg/day, 225 times the maximum recommended daily dose of Iloprost on a mg/m^2basis.

14 CLINICAL STUDIES

14.1 Frostbite

The efficacy of intravenous (IV) iloprost for the treatment of severe frostbite to reduce the risk of digit amputations is derived from a published open-label, randomized controlled trial that enrolled patients with severe frostbite (Cauchy et al, 2011; Cheguillaume, 2011) [Cauchy, E., et al. (2011). A controlled trial of a prostacyclin and rt-PA in the treatment of severe frostbite. N Engl J Med 364, 189-190; Cheguillaume, B. (2011). Controlled trial of iloprost and iloprost and rt-PA in the treatment of severe frostbite. Grenoble School of Medicine Thesis. HAL, https://dumas.ccsd.cnrs.fr/dumas-00618697.] . Severe frostbite was defined as having at least one digit (finger or toe) with frostbite stage 3 (lesion extending just past the proximal phalanx) or stage 4 (lesion extending proximal to the metacarpal or metatarsal joint).

The trial randomized 47 patients at a single site between 1996 and 2008. At enrollment, all eligible patients (n=47) were treated with rapid rewarming of areas with frostbite, aspirin 250 mg IV, and buflomedil 400 mg IV and then randomized to Groups A, B or C. All patients continued to receive aspirin 250 mg IV daily up to 8 days. In addition, Group A (n=15) received buflomedil 400 mg IV for up to 8 days, Group B (n=16) received iloprost IV for 6 hours daily for up to 8 days, and Group C (n=16) received recombinant tissue plasminogen activator IV on Day 1 and iloprost IV for 6 hours daily for up to 8 days.

The mean age of the study population was 33 years (range: 18-55 years), 94% were men, 96% sustained frostbite during sports activities, 6% had history of smoking, and none had diabetes. At randomization, 70% of the patients had frostbite involving the feet, 62% had frostbite involving the hands, and 32% had frostbite involving both feet and hands.

The primary endpoint was the presence of an anomaly (absence of uptake) in the bone phase of technetium 99m scan performed 7 days after initial clinical presentation of frostbite (BS2 bone scintigraphy anomaly) in at least one finger/toe affected by severe frostbite. The BS2 bone scintigraphy anomaly is expected to predict risk of amputation.

On day 7, the presence of BS2 bone scintigraphy anomaly was observed in 60% (9/15), 0% (0/16) and 19% (3/16) of the patients in Groups A, B, and C, respectively. Compared to Group A, the presence of bone scintigraphy anomaly was significantly lower in Group B (p < 0.001) and Group C (p<0.03), favoring iloprost.

Additional follow-up data confirming amputation were obtained for 40/47 patients, which was concordant with the bone scintigraphy results.

16 HOW SUPPLIED/STORAGE AND HANDLING

AURLUMYN (iloprost) injection is a clear, colorless sterile solution supplied as 100 mcg per mL single-dose glass vial per carton (NDC 50633-340-01).

STORAGE AND HANDLING

Unopened vials of AURLUMYN are stable until the date indicated on the package when stored at 20°C to 25°C (68°F to 77°F), with excursions permitted to 15°C to 30°C (59°F to 86°F) [see USP Controlled Room Temperature].

The unopened vial should be kept in the carton and not exposed to direct sunlight. Do not freeze.

17 PATIENT COUNSELING INFORMATION

Advise patients that they may have a fall in blood pressure with AURLUMYN, so they may become dizzy during drug administration. They should stand up slowly when they get out of a chair or bed.

Manufactured for:

BTG International Inc

West Conshohocken, PA 19428

Made in USA

SERB® and the SERB logo are registered trademarks of SERB S.à.r.l.

AURLUMYN™ is a trademark of SERB S.à.r.l., licensed by BTG International Inc.,

a SERB company.

©2024 BTG International Inc. All rights reserved